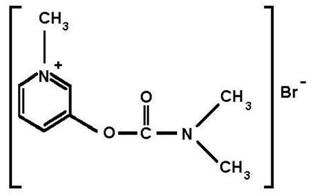 DRUG LABEL: Unknown
Manufacturer: Valeant Canada Limited
Category: prescription | Type: HUMAN PRESCRIPTION DRUG LABEL WITH HIGHLIGHTS
Date: 20081027

HIGHLIGHTS OF PRESCRIBING INFORMATION

CAUTION: USE AS A PRETREATMENT ONLY - USE ATROPINE AND 2-PAM AFTER SOMAN EXPOSURE - USE PROTECTIVE GARMENTS

CAUTION: USE AS A PRETREATMENT ONLY - USE ATROPINE AND 2-PAM AFTER SOMAN EXPOSURE - USE PROTECTIVE GARMENT(S)

See full prescribing information for complete boxed warning.

- Pyridostigmine bromide is for use as a pretreatment for exposure to the chemical nerve agent Soman. Pyridostigmine alone will not protect against exposure to Soman. The efficacy of pyridostigmine is dependent upon the rapid use of atropine and pralidoxime (2-PAM) after Soman exposure.
- Primary protection against exposure to chemical nerve agents is the wearing of protective garments.
- Pyridostigmine must not be taken after exposure to Soman. If taken immediately before Soman exposure (e.g., when the gas attack alarm is given) or at the same time as poisoning by Soman, it is not expected to be effective, and may exacerbate the effects of a sub-lethal exposure to Soman.

1 INDICATIONS AND USAGE

Pyridostigmine bromide is a reversible cholinesterase inhibitor indicated for pretreatment against the lethal effects of soman nerve agent poisoning. (1)

Pyridostigmine bromide is for use in conjunction with

- Protective garments, including a gas mask, and
- Immediate atropine and pralidoxime therapy at the first sign of nerve agent poisoning. (1)

2 DOSAGE AND ADMINISTRATION

- One 30 mg tablet every 8 hours. (2)
- Start at least several hours prior to exposure to Soman. (2)
- At the first sign of Soman poisoning pyridostigmine must be stopped, and atropine and 2-PAM be administered. (2)
- Use beyond 14 consecutive days should be evaluated in the context of the likelihood of Soman exposure. (2)
- Store refrigerated between 2 and 8°C (36-46°F). Protect from light. Do not dispense after removal from refrigeration for more than a total of 3 months. (16)

3 DOSAGE FORMS AND STRENGTHS

- 30 mg tablets (round, white imprinted with letters "PBT") (3)

4 CONTRAINDICATIONS

- Mechanical intestinal or urinary obstruction. (4)
- Known hypersensitivity to anticholinesterase agents. (4)

5 WARNINGS AND PRECAUTIONS

- At the first sign of Soman poisoning pyridostigmine must be stopped, atropine and 2-PAM must be administered immediately. (5.1)
- Use with caution in persons with increased risk of anticholinergic reactions, such as persons with bronchial asthma, chronic obstructive pulmonary disease, bradycardia, cardiac arrhythmias, beta blocker treatment (increased risk of anticholinergic reactions). (5.2)
- Use with caution in persons with bromide sensitivity. (5.3)
- In case of serious adverse reactions, advise personnel to temporarily discontinue pyridostigmine and seek immediate medical attention. (5.4)

6 ADVERSE REACTIONS

Most common adverse reactions (≥ 3%) are diarrhea, abdominal pain, dysmenorrhea, and twitch. (6)

7 DRUG INTERACTIONS

- Mefloquine: Additive effect on gastrointestinal tract and atrial rate. (7.1)
- Anticholinesterase drugs for glaucoma treatment: Additive effects. (7.2)
- Narcotics: Exacerbation of bradycardia possible. (7.3)
- Depolarizing neuromuscular blocking agents: Increased effect. (7.4)
- Non-depolarizing neuromuscular blocking agents: Dose may need to be increased. (7.4)
- Aminoglycoside antibiotics, local and some general anesthetics, antiarrhythmic agents, and other drugs that interfere with neuromuscular transmission should be used cautiously, if at all. (7.4)
- Drugs converted to pantothenic acid (e.g., dexpanthenol): Additive effect. (7.5)

8 USE IN SPECIFIC POPULATIONS

- Renal impairment: Increased risk of side effects; careful dose selection. In persons with renal impairment, renal function monitoring may be useful. (8.6)

FULL PRESCRIBING INFORMATION

CAUTION: USE AS A PRETREATMENT ONLY - USE ATROPINE AND 2-PAM AFTER SOMAN EXPOSURE - USE PROTECTIVE GARMENTS

- Pyridostigmine bromide is for use as a pretreatment for exposure to the chemical nerve agent Soman. Pyridostigmine alone will not protect against exposure to soman. The efficacy of pyridostigmine is dependent upon the rapid use of atropine and pralidoxime (2-PAM) after Soman exposure. [See Dosage and Administration (2)]
- Primary protection against exposure to chemical nerve agents is the wearing of protective garments including masks, hoods and overgarments designed specifically for this use.
  Individuals must not rely solely upon pretreatment with pyridostigmine and on the antidotes atropine and pralidoxime (2-PAM) to provide complete protection from poisoning by the chemical nerve agent Soman.
- Pyridostigmine must not be taken after exposure to Soman. If pyridostigmine is taken immediately before exposure (e.g., when the gas attack alarm is given) or at the same time as poisoning by Soman, it is not expected to be effective, and may exacerbate the effects of a sub-lethal exposure to Soman. [See Clinical Pharmacology (12.2)]

FOR MILITARY MEDICAL USE ONLY

1 INDICATIONS AND USAGE

Pyridostigmine bromide is indicated for pretreatment against the lethal effects of Soman nerve agent poisoning. Pyridostigmine is intended for use in conjunction with protective garments, including a mask. At the first sign of nerve agent poisoning, pyridostigmine should be stopped, and atropine and pralidoxime therapy started immediately.

The evidence for the effectiveness of pyridostigmine as pretreatment against Soman-induced toxicity was derived from animal studies alone [see Nonclinical Toxicology (13.2)].

FOR MILITARY MEDICAL USE ONLY

2 DOSAGE AND ADMINISTRATION

PYRIDOSTIGMINE BROMIDE IS FOR USE AS A PRETREATMENT FOR EXPOSURE TO THE CHEMICAL NERVE AGENT SOMAN. PYRIDOSTIGMINE ALONE WILL NOT PROTECT AGAINST EXPOSURE TO SOMAN. THE EFFICACY OF PYRIDOSTIGMINE IS DEPENDENT UPON THE RAPID USE OF ATROPINE AND PRALIDOXIME (2-PAM) AFTER SOMAN EXPOSURE.

PRIMARY PROTECTION AGAINST EXPOSURE TO CHEMICAL NERVE AGENTS IS THE WEARING OF PROTECTIVE GARMENTS INCLUDING MASKS, HOODS AND OVERGARMENTS DESIGNED SPECIFICALLY FOR THIS USE.

INDIVIDUALS MUST NOT RELY SOLELY UPON PRETREATMENT WITH PYRIDOSTIGMINE, AND THE ANTIDOTES ATROPINE AND PRALIDOXIME (2-PAM) TO PROVIDE COMPLETE PROTECTION FROM POISONING BY THE CHEMICAL NERVE AGENT SOMAN.

PYRIDOSTIGMINE MUST NOT BE TAKEN AFTER EXPOSURE TO SOMAN. IF PYRIDOSTIGMINE IS TAKEN IMMEDIATELY BEFORE EXPOSURE (E.G., WHEN THE GAS ATTACK ALARM IS GIVEN) OR AT THE SAME TIME AS POISONING BY SOMAN, IT IS NOT EXPECTED TO BE EFFECTIVE, AND MAY EXACERBATE THE EFFECTS OF A SUB-LETHAL EXPOSURE TO SOMAN [See Clinical Pharmacology (12.2)].

The dose of pyridostigmine is one 30 mg tablet every 8 hours, started at least several hours prior to exposure to Soman. At the first sign of nerve agent poisoning, pyridostigmine should be discontinued and treatment with atropine and pralidoxime should be instituted immediately.

There is no known advantage to taking pyridostigmine just prior to or concurrent with Soman exposure. According to the mechanism of action of pyridostigmine described below [See Clinical Pharmacology (12.2)], pyridostigmine should be effective when it is given sufficiently in advance of Soman poisoning to provide a pool of protected enzyme. Therefore, it is expected that pyridostigmine will not be effective if administered just prior to or during exposure to Soman.

The benefits and risks of use beyond 14 consecutive days have not been definitively established, therefore, continued use beyond 14 consecutive days should be evaluated in the context of the likelihood of exposure to Soman nerve agent.

3 DOSAGE FORMS AND STRENGTHS

Pyridostigmine Bromide Tablets, USP, 30 mg, are round, white and imprinted with the letters "PBT"

4 CONTRAINDICATIONS

- Mechanical intestinal or urinary obstruction
- Known hypersensitivity to anticholinesterase agents

5 WARNINGS AND PRECAUTIONS

5.1 Stopping Pyridostigmine and Using Atropine and 2-PAM in the Event of Soman Exposure

See Dosage and Administration (2) and Boxed Caution statement (at beginning of Full Prescribing Information).

Pyridostigmine pretreatment offers no benefit against the nerve agent Soman unless the nerve agent antidotes atropine and pralidoxime (2-PAM) are administered once symptoms of poisoning appear. Pyridostigmine should be discontinued at the first sign of nerve agent poisoning since it may exacerbate the effects of a sub-lethal exposure to Soman.

5.2 Individuals at Increased Risk of Anticholinergic Adverse Reactions

Pyridostigmine should be used with caution in persons with bronchial asthma, chronic obstructive pulmonary disease, bradycardia, cardiac arrhythmias, and, for example, in people being treated for hypertension or glaucoma with beta adrenergic receptor blockers.

5.3 Use in Bromide-Sensitive Individuals

Caution should be taken when administering pyridostigmine bromide to individuals with known bromide sensitivity. The risks and benefits of administration must be weighed against the potential for rash or other adverse reactions in these individuals. [See Adverse Reactions (6)]

5.4 Action in Case of Serious Adverse Reactions

If personnel experience serious adverse reactions such as difficult breathing, severe dizziness, or loss of consciousness as a result of ingestion of pyridostigmine bromide, they should be advised to temporarily discontinue use of product and seek immediate medical attention. Serious adverse events should be reported to their commander and responsible medical officer.

6 ADVERSE REACTIONS

The most common adverse reactions (≥ 3%) are diarrhea, abdominal pain, dysmenorrhea, and twitch.

The adverse reactions to pyridostigmine bromide are typically of two varieties, muscarinic and nicotinic. Muscarinic adverse reactions include abdominal cramps, bloating, flatulence, diarrhea, emesis, increased peristalsis, nausea, hypersalivation, urinary incontinence, increased bronchial secretion, diaphoresis, miosis, and lacrimation. Nicotinic adverse reactions are comprised chiefly of muscle cramps, fasciculations, and weakness.

Pyridostigmine is a quaternary ammonium compound and does not readily cross the blood-brain barrier. Compared to the peripheral effects of pyridostigmine bromide, central nervous system manifestations are less frequent and less serious, primarily consisting of headache and vertigo, with minor and clinically insignificant changes in heart rate, blood pressure, and respiratory function.

Extremely high doses may produce CNS symptoms of agitation, restlessness, confusion, visual hallucinations, and paranoid delusions. Electrolyte abnormalities, possibly resulting from high serum bromide concentrations, also have been reported. Death may result from cardiac arrest or respiratory paralysis and pulmonary edema.

As with any compound containing bromide, a skin rash may be observed in an occasional patient, which usually subsides promptly upon discontinuance of the medication.

6.1 Clinical Studies Experience

In a controlled study of 90 healthy volunteers comparing pyridostigmine 30 mg every 8 hours to placebo for 21 days, the following incidence of adverse reactions was reported.

Table 1 Incidence of Adverse Reactions ≥ 2%
Reaction: | % Pyridostigmine N = 60 | % Placebo N = 30
Diarrhea | 7 | 0
Abdominal Pain | 7 | 0
Dysmenorrhea | 5 | 0
Twitch | 3 | 0
Myalgia | 2 | 0
Dry Skin | 2 | 0
Urinary Frequency | 2 | 0
Epistaxis | 2 | 0
Amblyopia | 2 | 0
Hypesthesia | 2 | 0
Neck pain | 2 | 0

Other less common adverse reactions seen during controlled and uncontrolled clinical trials for pyridostigmine include the following:

- Pulmonary: Exacerbation of acute bronchitis and asthma
- Cardiovascular: Elevated blood pressure, decreased heart rate (4-6 beats per minute), chest tightness
- Eyes: Change in vision, eye pain
- Neurologic: Headache, hypertonia, difficulty in concentrating, confusion, disturbed sleep, tingling of extremities, numbness of the tongue
- Skin: Increased sweating, rash, alopecia
- Digestive: Vomiting, borborygmi, nausea, bloating, flatulence
- General: Warm sensation, lethargy/drowsiness, depressed mood

During safety studies at the recommended dosage, there were two reports of loss of consciousness, one of which also included urinary and fecal incontinence, stiffness of the upper torso and arms, post-syncopal skin pallor, post-syncopal confusion, and post-syncopal weakness (suggesting a seizure event).

7 DRUG INTERACTIONS

7.1 Mefloquine

A potential interaction between the antimalarial drug mefloquine and pyridostigmine bromide exists through a possible additive effect on the gastrointestinal tract. The most common complaint about both drugs is loose bowels. It has been reported that simple additive effects on the atrial rate occur when mefloquine and pyridostigmine bromide are combined.

7.2 Other Anticholinesterase Drugs

Because anticholinesterase drugs are often used in the treatment of glaucoma, the use of pyridostigmine bromide in such situations may have an additive effect that may cause or exacerbate problems with night vision.

7.3 Narcotics

The bradycardia associated with the use of narcotics may exacerbate pyridostigmine-induced bradycardia.

7.4 Drugs that Interfere with Neuromuscular Transmission

Particular caution should be observed in the administration of depolarizing neuromuscular blocking agents (e.g., succinylcholine) during surgery since the degree of neuromuscular blockade that ensues may be enhanced by previously administered pyridostigmine bromide. Doses of non-depolarizing neuromuscular blocking agents (e.g., pancuronium bromide) may need to be increased in patients previously administered pyridostigmine. Atropine antagonizes the muscarinic effects of pyridostigmine, and this interaction is utilized to counteract the muscarinic symptoms of pyridostigmine toxicity. Anticholinesterase agents are sometimes effective in reversing neuromuscular block induced by aminoglycoside antibiotics. However, aminoglycoside antibiotics, local and some general anesthetics, antiarrhythmic agents, and other drugs that interfere with neuromuscular transmission should be used cautiously, if at all.

7.5 Drugs Converted to Pantothenic Acid (e.g., Dexpanthenol)

Theoretically, drugs such as dexpanthenol, which are converted to pantothenic acid in vivo, may have additive effects with pyridostigmine by increasing production of acetylcholine.

8 USE IN SPECIFIC POPULATIONS

8.1 Pregnancy

TERATOGENIC EFFECTS

Pregnancy Category B

Pyridostigmine produced no teratogenic effects in rats given up to 30 mg/kg/day and in rabbits given up to 45 mg/kg/day orally during the period of organogenesis. These doses are 3 and 10 times, respectively, the recommended human dose of 90 mg on a mg/m^2 basis. In rats, a slight degree of delayed skeletal ossification was seen at 30 mg/kg, a dose which caused maternal toxicity, and a slight increase in the incidence of hydronephrosis was seen at all dose levels (lowest dose tested was 3 mg/kg). In rabbits, a slight increase in the incidence of hydronephrosis was seen at 45 mg/kg, a dose which caused maternal toxicity, and increased incidences of blood vessel variations were seen at all doses (lowest dose tested was 5 mg/kg). There are no adequate and well-controlled studies in pregnant women. Because animal reproduction studies are not always predictive of human response, this drug should be used during pregnancy only if clearly needed.

8.3 Nursing Mothers

It is not known whether this drug is excreted in human milk. Because many drugs are excreted in human milk caution should be exercised when pyridostigmine is administered to a nursing woman.

8.4 Pediatric Use

Safety and effectiveness in pediatric patients have not been established.

8.5 Geriatric Use

Clinical studies of pyridostigmine did not contain sufficient numbers of subjects aged 65 and over to determine whether they respond differently from younger subjects. In general, dose selection for an elderly patient should be cautious, reflecting the greater frequency of decreased hepatic, renal, or cardiac function, and of concomitant disease or other drug therapy.

In the elderly (71-85 years of age) the elimination half-life, volume of distribution (central and steady state) were comparable with the young (21-51 years of age). However, the systemic plasma clearance was significantly lower in the elderly compared to the young (6.7 ± 2.2 vs. 9.5 ± 2.7 ml/min/kg).

This drug is known to be substantially excreted by the kidney, and the risk of toxic reactions to this drug may be greater in patients with impaired renal function. Because elderly patients are more likely to have decreased renal function, care should be taken in dose selection, and it may be useful to monitor renal function.

8.6 Persons with Renal Impairment

This drug is known to be substantially excreted by the kidney, and the risk of toxic reactions to this drug may be greater in patients with impaired renal function. Caution should be observed, and dosage be selected carefully, when administering pyridostigmine bromide to patients with impaired renal function. In anephric patients, a 3-fold increase in the elimination half-life and a 75% decrease in systemic clearance was observed [see Clinical Pharmacology (12.3)] It may be useful to monitor renal function.

8.7 Persons with Hepatic Impairment

No information is available on the pharmacokinetics of pyridostigmine in hepatic impaired patients.

9 DRUG ABUSE AND DEPENDENCE

9.2 Abuse

Although the abuse potential of pyridostigmine has not been specifically assessed, no abuse of, tolerance to, withdrawal from, or drug-seeking behavior was observed in patients who received pyridostigmine in clinical trials. Cholinesterase inhibitors are not believed to be associated with drug abuse.

10 OVERDOSAGE

As is true of all cholinergic drugs, overdosage of pyridostigmine bromide may result in cholinergic crisis, a state characterized by increasing muscle weakness that, through involvement of the muscles of respiration, may lead to death. Overdosage with pyridostigmine must be differentiated from the acute manifestations of nerve agent poisoning which may also be characterized by a cholinergic crisis. Atropine should be used to treat pyridostigmine overdosage.

In the treatment of pyridostigmine overdosage, maintaining adequate respiration is of primary importance. Tracheostomy, bronchial aspiration, and postural drainage may be required to maintain an adequate airway; respiration can be assisted mechanically if required. Supplemental oxygen may be necessary. Pyridostigmine should be discontinued immediately and 1-4 mg of atropine sulfate administered i.v. Additional doses of atropine may be given every 5-30 minutes as needed to control muscarinic symptoms. Atropine overdosage should be avoided, as tenacious secretions and bronchial plugs may result. It should be kept in mind that unlike muscarinic effects, the skeletal muscle effects and consequent respiratory paralysis (nicotinic effects) which can occur following pyridostigmine overdosage are not alleviated by atropine.

11 DESCRIPTION

Pyridostigmine bromide is an orally active, reversible cholinesterase inhibitor. Its chemical name is: 3-hydroxy-1-methylpyridinium bromide dimethylcarbamate.

CAS registration number is 101-26-8.

Pyridostigmine bromide has a molecular formula of C9H13BrN202, a molecular weight of 261.12, and the following molecular structure:

Pyridostigmine bromide tablets, USP contain 30 mg pyridostigmine bromide for oral administration. The inactive ingredients included in the tablet formula are: lactose anhydrous, colloidal silicon dioxide, and stearic acid.

12 CLINICAL PHARMACOLOGY

12.1 Mechanism of Action

Pyridostigmine is a reversible cholinesterase inhibitor.

12.2 Pharmacodynamics

The mechanism of Soman induced death is reasonably well-understood; death is believed to result primarily from respiratory failure due to irreversible inhibition of the enzyme acetylcholinesterase and the consequent increase in the level of the neurotransmitter acetylcholine 1) at nicotinic receptors at the neuromuscular junction, resulting in pathological stimulation and ultimate failure of the muscles of respiration, 2) at muscarinic receptors in secretory glands and smooth muscle, resulting in excessive respiratory secretions and bronchoconstriction, and 3) at cholinergic receptors in the brain, resulting in central respiratory depression.

The effect of pyridostigmine is presumed to result from its reversible inhibition of a critical number of acetylcholinesterase active sites in the peripheral nervous system, protecting them from irreversible inhibition by Soman. (Pyridostigmine is not thought to enter the brain in significant amounts.) When the pyridostigmine-induced inhibition of the enzyme is subsequently reversed, there is a small residual amount of enzyme activity that is adequate to sustain life (provided atropine and 2-PAM are subsequently administered). An implication of this presumed mechanism is that it is not helpful to give pyridostigmine either just before or during exposure to Soman.

12.3 Pharmacokinetics

Pyridostigmine bromide is poorly absorbed from the gastrointestinal tract with an absolute bioavailability of 10-20%. Following a single oral dose of 30 mg pyridostigmine bromide in the fasting state, the TMAX was 2.2 ± 1.0 hours. The pharmacokinetics of pyridostigmine bromide is linear over the dose range of 30-60 mg. Following multiple doses of pyridostigmine (30 mg every 8 hours for 21 days), the average steady-state trough concentration of pyridostigmine was about ¼ of the peak concentration after a single dose.

The volume of distribution was about 19 ± 12 liters, indicating that pyridostigmine distributes into tissues. No information on protein binding of pyridostigmine is available.

Pyridostigmine undergoes hydrolysis by cholinesterases and is metabolized in the liver. It is excreted in the urine both as unchanged drug and its metabolites. The systemic clearance of pyridostigmine bromide is 830 mL/min and the elimination half-life of pyridostigmine bromide is approximately 3 hours.

Renal Impairment

In anephric patients (n=4), the elimination half-life increased 3 fold and the systemic clearance decreased by 75% [see Use in Specific Populations (8.6)].

Hepatic Impairment

No information is available on the pharmacokinetics of pyridostigmine in hepatic impaired patients.

Gender

The clearance of pyridostigmine bromide is not influenced by gender.

Elderly

In a pyridostigmine study in the elderly (71-85 years), the elimination half-life of pyridostigmine was similar to the half-life in the young (21-51 years). However, the systemic plasma clearance was 30% lower in the elderly.

13 NONCLINICAL TOXICOLOGY

13.1 Carcinogenesis, Mutagenesis, Impairment of Fertility

Carcinogenicity

No long-term studies to evaluate carcinogenicity have been performed in animals.

Mutagenicity

Pyridostigmine was mutagenic and clastogenic in an in vitro mammalian gene mutation assay in mouse lymphoma cells, in the presence of metabolic activation only. Pyridostigmine was not mutagenic in an in vitro bacterial reverse mutation assay (Ames Test) and in an in vitro mammalian gene mutation assay in Chinese hamster ovary cells, and was not clastogenic in an in vitro assay in Chinese hamster ovary cells or in an in vivo mouse micronucleus assay.

Impairment of Fertility

Pyridostigmine did not impair fertility in male and female rats given oral doses of up to 45 mg/kg/day (5 times the recommended human daily dose of 90 mg on a mg/m^2 basis) beginning at 10 (males) or 2 (females) weeks prior to mating.

13.2 Animal Toxicology and/or Pharmacology

Evidence of the effectiveness of pyridostigmine as a pre-treatment for Soman poisoning was obtained from studies in animals alone, because it is clearly unethical to perform such studies in humans. While the results of these animal studies cannot be extrapolated to humans with certainty, the extrapolation is supported by the reasonably well understood pathophysiologic mechanisms of the toxicity of Soman and the mechanism of the protective effect of pyridostigmine pretreatment, as examined in various animal species. In addition, the results of these animal studies establish that pyridostigmine is reasonably likely to produce clinical benefit in humans. The section below explains the current understanding of the mechanism of Soman toxicity and the beneficial effect of pyridostigmine pretreatment, as well as the basis for extrapolating the animal findings to humans.

Pyridostigmine pretreatment has been shown in animals to decrease the lethality of the nerve agent Soman, provided atropine and pralidoxime (2-PAM) are administered immediately after exposure to Soman.

Rhesus monkeys were given oral doses of pyridostigmine every 8 hours for a total of 6 doses, and were challenged with Soman given intramuscularly 5 hours after the last pyridostigmine dose. Two dosage groups of pyridostigmine were used: a low dose group given 1.2 mg/kg for all 6 doses, and a high dose group given 1.2 and 1.8 mg/kg for the first and second doses, respectively, and 2.4 mg/kg for the final 4 doses. These animals were also given atropine and 2-PAM after exposure to Soman. An untreated control group, and a group given atropine and 2-PAM (but not pyridostigmine), were also used. The primary endpoint in this study was a decrease in the lethality of Soman expressed as an increase in the LD 50 (the dose of Soman that killed 50 % of the animals). The atropine/2-PAM control group showed a small but statistically significant 1.6 fold increase in the Soman LD 50 compared to the untreated control group. The groups given pyridostigmine as well as atropine and 2-PAM showed increases in the Soman LD 50 of at least 40 fold compared to the untreated control group and at least 25 fold compared to the atropine/2-PAM group. The two dose levels of pyridostigmine showed similar effectiveness.

Additional studies in rhesus monkeys and guinea pigs also showed effectiveness of pyridostigmine (in the presence of post-Soman administration of atropine and 2-PAM). The magnitude of effect in guinea pigs was smaller than that in monkeys (Soman LD 50 increased 4-7 fold compared to untreated control and 2-4 fold compared to atropine/2-PAM alone). Pyridostigmine produced only small and inconsistent effects in studies in rats, mice and rabbits. It is thought that the effect of pyridostigmine in rats and mice is masked by high blood levels of the enzyme carboxylesterase, which eliminates Soman from blood and makes those species highly resistant to Soman. In a study in which rats were given an inhibitor of carboxylesterase, pretreatment with pyridostigmine plus atropine increased the LD 50 of Soman 8.5 fold compared to untreated controls. Humans have little or no carboxylesterase in blood.

Animal studies have shown that pyridostigmine pretreatment was effective only when animals were given atropine and 2-PAM after exposure to Soman.

14 CLINICAL STUDIES

Evidence of the effectiveness of pyridostigmine as a pretreatment for Soman poisoning was obtained from studies in animals alone, because it is clearly unethical to perform such studies in humans.

16 HOW SUPPLIED/STORAGE AND HANDLING

Pyridostigmine bromide tablets, USP, 30 mg, are round, white tablets imprinted with the letters "PBT".

Immediate Container: Twenty-one (21) tablets individually sealed in a blister or strip package which is supplied in a protective sleeve.

NDC: 46594-750-01

NSN 6505-01-178-7903 [The NSN refers to the actual unit that is ordered from supply (if someone orders 1 of this stock number they will get one Mylar bag as a unit of issue (or one package of 10 blister packs). The exterior carton lists the NSN and the description of the product that the NSN applies to and lists 10 PG (packages) as the quantity within the carton.]

Storage

Store refrigerated between 2 and 8°C (36-46°F). Protect from light.

Do not dispense the content of unit packages (10 blister packs) and shipping containers (10 packages of 10 each blister packs) after removal from refrigeration for more than a total of 3 months. Do not use after the 10 year expiration date provided on the package. Military personnel should be advised to discard the contents of the individual unit packages of pyridostigmine 3 months after issue.

17 PATIENT COUNSELING INFORMATION

Pyridostigmine Bromide Tablets, USP, are supplied with a Patient Information Sheet.

Personnel should be instructed to read the Patient Information Sheet before using Pyridostigmine Bromide (PB) Tablets.

The following information and advice should be discussed with personnel when PB is issued.

17.1 Indication and Conditions of Use

- Pyridostigmine bromide is approved as a pretreatment for protection against the chemical nerve agent Soman (GD). PB has not been approved for use against other chemical nerve agents including Sarin (GB), Tabun (GA), and VX. [See Indications and Usage (1)]
The approval is based on safety studies in humans and effectiveness studies conducted in animals. The FDA has approved PB based only on animal studies of effectiveness because it is not ethical to do these studies in humans. Human studies would require exposing people to the deadly effects of nerve agents, risking poisoning them or even killing them. Studies in monkeys and guinea pigs show that pretreatment with PB makes the antidotes (atropine and 2-PAM) work better against Soman (GD). [See Nonclinical Toxicology (13.2)]
- The main protection against chemical weapons is the chemical protective mask and battle dress overgarments [see boxed CAUTION and Dosage and Administration (2)].
- Pyridostigmine bromide is used as a pretreatment against a Soman nerve agent attack. Based on the animal studies, it is thought that any potential benefits from use of PB occur only if:
  (1) It is taken within 8 hours before, but not right before, exposure to the nerve agent Soman. If it is taken right before (when the nerve gas attack alarm is given) or during nerve agent exposure, it may not work and may make the effects of Soman worse.
  (2) Atropine and 2-PAM are used when symptoms of nerve agent poisoning occur. The two antidotes are part of the MARK I Nerve Agent Antidote Kit or the ATNAA (Antidote Treatment – Nerve Agent Autoinjector).

See Dosage and Administration (2).

17.2 Dosage and Administration

1. The chain of command will tell personnel when it is time to take PB, based on the threat of exposure to Soman nerve agents.
2. One tablet must be taken every 8 hours until the chain of command tells personnel to stop taking PB.
3. PB tablets must not be taken more often. The dose must not be doubled if a dose has been missed.
4. There is no known advantage to taking extra PB right before Soman exposure.
5. No further PB should be taken after nerve agent exposure has occurred, instead:
6. Persons experiencing most or all of the MILD symptoms of nerve agent poisoning, should IMMEDIATELY hold their breath (AVOID INHALATION) AND PUT ON THEIR PROTECTIVE MASK. Then atropine and 2-PAM (one MARK I kit or one ATNAA) must be administered.

See Dosage and Administration (2).

Personnel should contact their unit medical officer if adverse reactions from PB continue and limit duty performance.

17.3 Contraindications and Precautions

Pyridostigmine bromide must not be taken by persons with

- mechanical bowel or bladder obstruction
- hypersensitivity to anticholinesterase medicines (certain drugs used during surgery like physostigmine, edrophonium, neostigmine, and ambenonium)

See Contraindications (4).

Personnel should be instructed to inform their doctor or medic before taking PB if they:

- are pregnant
- have asthma
- are allergic to bromide
- take a beta blocker (a medicine to treat, e.g., high blood pressure)
- have high eye pressure (glaucoma)
- have any other medical condition, including heart problems or reflux esophagitis (GERD)

See Warnings and Precautions (5.2).

17.4 Side Effects (Adverse Reactions)

- Stomach cramps
- Gas
- Diarrhea
- Nausea
- Frequent urination
- Increased salivation
- Sweating
- Headaches
- Dizziness
- Watery eyes
- Blurred vision
- Runny nose
- Difficulty or tightness in breathing
- Acid stomach (including heartburn or reflux)
- Tingling of fingers, toes, arms, and legs
- Muscle twitching or weakness
- Muscle cramps

This list of adverse reactions is not complete.

See Adverse Reactions (6).

Most side effects are mild and will disappear without treatment.

Pyridostigmine bromide has been safely used and has been FDA approved for over 40 years in the U.S. to treat a disease called myasthenia gravis (MG). Human studies of PB at doses intended for military use have found PB to be generally safe.

Personnel should contact their unit medical officer if side effects from PB continue and limit duty performance.

17.5 Collection of Information

DOD may collect information on the use of PB to help decide how best to protect deployed forces in the future. Information that identifies individual persons will remain confidential. However, the FDA may review any data collected by DOD for the purpose of evaluating PB.

17.6 Questions and Requests for Information

Questions about personnel rights and welfare should be directed to the unit medical officer, or e-mailed to usamrmcregulatoryaffairs@amedd.army.mil.

Personnel can receive information about PB from unit medical officers or medics. Questions about PB can also be e-mailed directly to the U.S. Army Medical Research and Materiel Command at address usamrmcregulatoryaffairs@amedd.army.mil.

Distributed by:
Defense Supply Center, Philadelphia
Medical Directorate
700 Robbins Ave
Philadelphia, PA 19111

For:
Office of The Surgeon General
U.S. Army Medical Materiel Development Activity
ATTN: MCMR-UMR
1430 Veterans Drive
Fort Detrick, MD 21702-5012